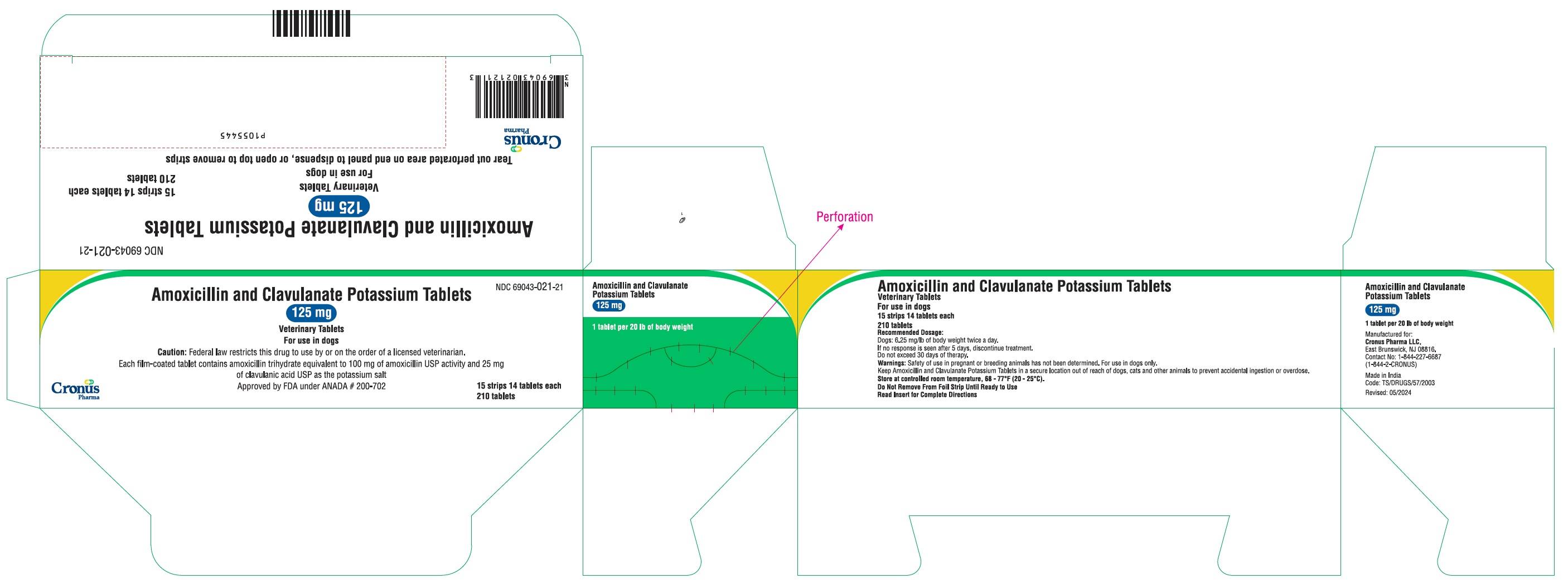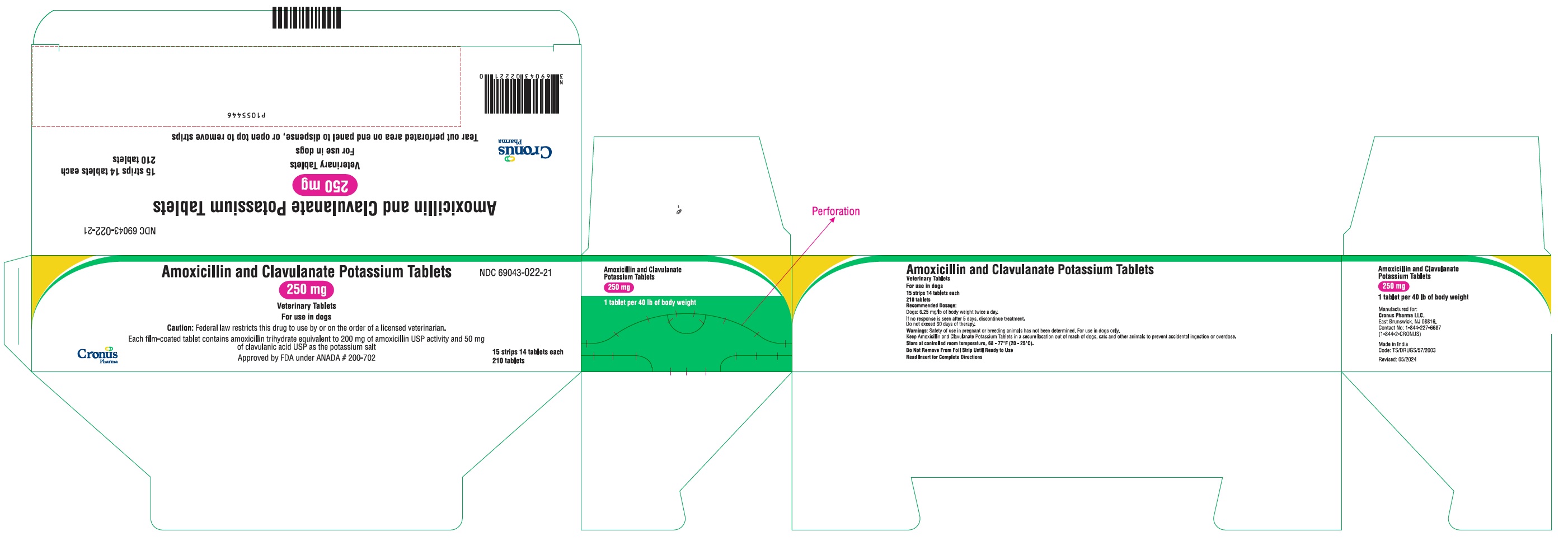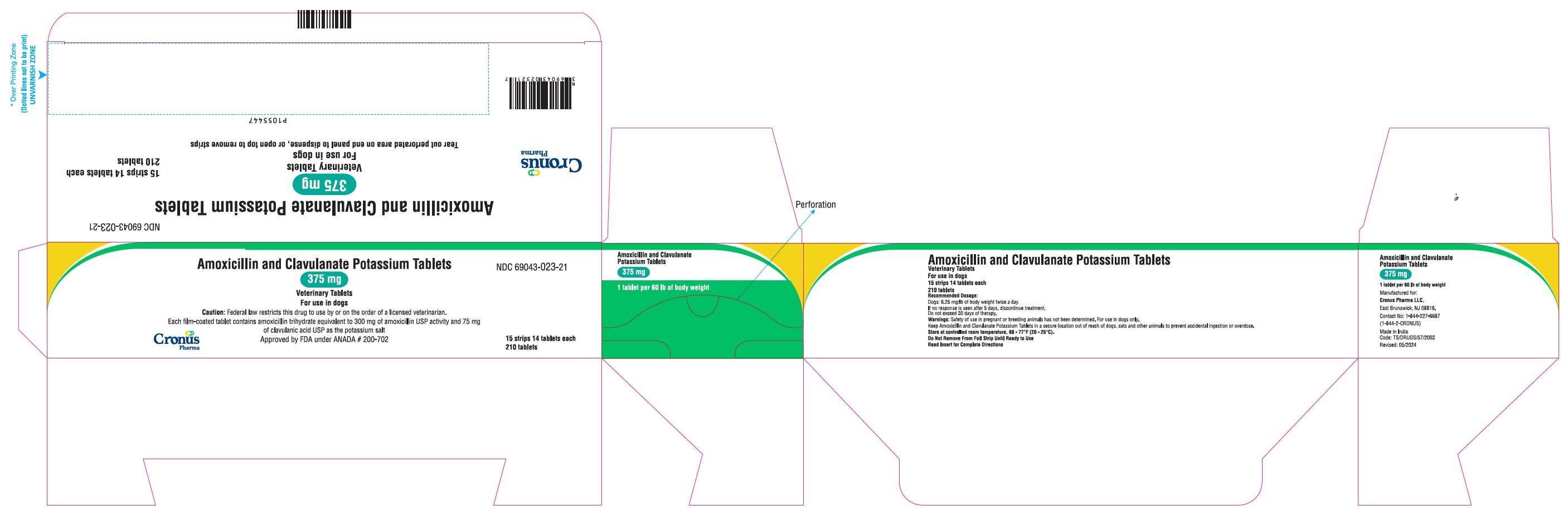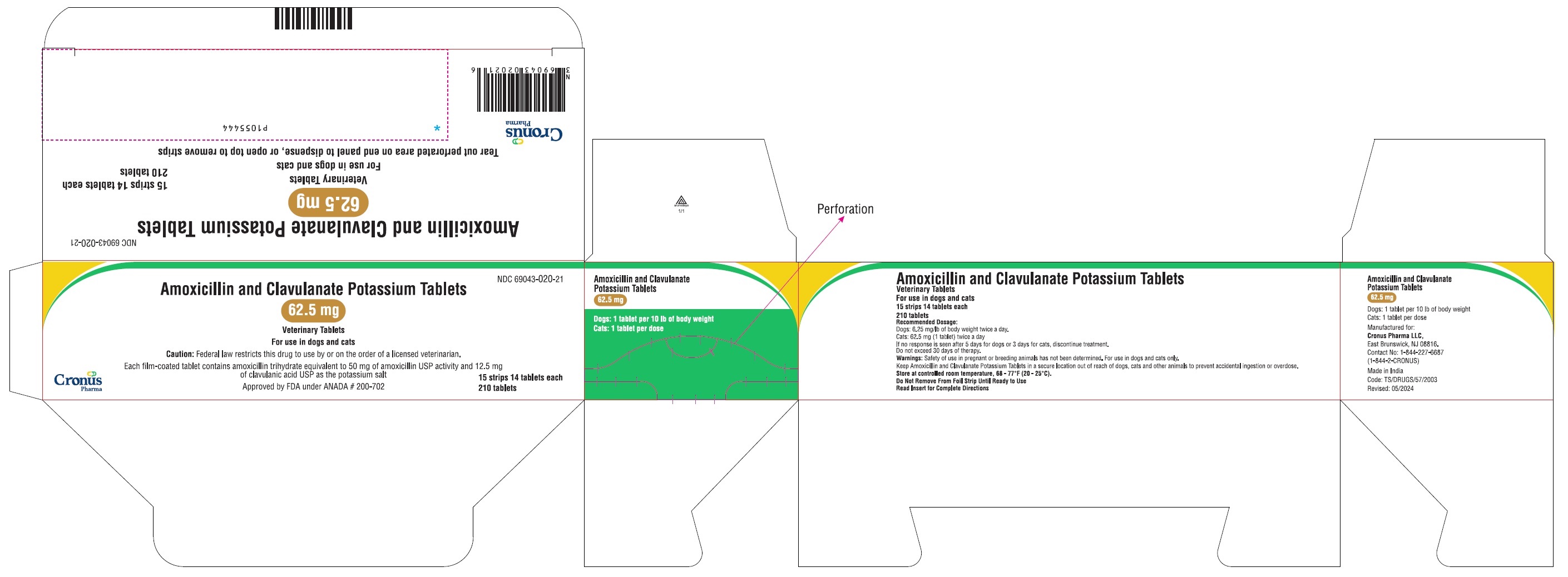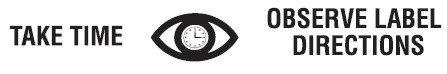 DRUG LABEL: Amoxicillin and Clavulanate Potassium
NDC: 69043-020 | Form: TABLET, COATED
Manufacturer: Cronus Pharma LLC
Category: animal | Type: PRESCRIPTION ANIMAL DRUG LABEL
Date: 20250530

ACTIVE INGREDIENTS: AMOXICILLIN 50 mg/1 1; CLAVULANATE POTASSIUM 12.5 mg/1 1

Amoxicillin and Clavulanate Potassium Tablets
Veterinary Tablets

WARNINGS AND PRECAUTIONS

For use in dogs and cats

CAUTION: Federal law restricts this drug to use by or on the order of a licensed veterinarian.

DESCRIPTION

DESCRIPTION: Amoxicillin and Clavulanate Potassium Tablets are an orally administered formulation comprised of the broad-spectrum antibiotic amoxicillin trihydrate and the β-lactamase inhibitor, clavulanate potassium (the potassium salt of clavulanic acid).

Amoxicillin trihydrate is a semisynthetic antibiotic with a broad spectrum of bactericidal activity against many gram-positive and gram-negative, aerobic and anaerobic microorganisms. It does not resist destruction by β-lactamases; therefore, it is not effective against β-lactamase-producing
bacteria. Chemically, it is D(-)-α-amino-p-hydroxybenzyl penicillin trihydrate.

Clavulanic acid, an inhibitor of β-lactamase enzymes, is produced by the fermentation of Streptomyces clavuligerus. Clavulanic acid by itself has only weak antibacterial activity. Chemically, clavulanate potassium is potassium z-(3R,5R)-2-β-hydroxyethylidene clavam-3-carboxylate.

ACTIONS: Amoxicillin and Clavulanate Potassium Tablets are stable in the presence of gastric acid and are not significantly influenced by gastric or intestinal contents. The 2 components are rapidly absorbed resulting in amoxicillin and clavulanic acid concentrations in serum, urine, and tissues similar to those produced when each is administered alone.

Amoxicillin and clavulanic acid diffuse readily into most body tissues and fluids with the exception of brain and spinal fluid, which amoxicillin penetrates adequately when meninges are inflamed. Most of the amoxicillin is excreted unchanged in the urine. Clavulanic acid’s penetration into spinal fluid is unknown at this time. Approximately 15% of the administered dose of clavulanic acid is excreted in the urine within the first 6 hours.

Amoxicillin and Clavulanate Potassium Tablets combine the distinctive properties of a broad-spectrum antibiotic and a β-lactamase inhibitor to
effectively extend the antibacterial spectrum of amoxicillin to include β-lactamase producing as well as non-β-lactamase-producing aerobic and
anaerobic organisms.

MICROBIOLOGY

MICROBIOLOGY: Amoxicillin is bactericidal in action and acts through the inhibition of biosynthesis of cell wall mucopeptide of susceptible organisms. The action of clavulanic acid extends the antimicrobial spectrum of amoxicillin to include organisms resistant to amoxicillin and other β-lactam antibiotics. Amoxicillin/clavulanate has been shown to have a wide range of activity which includes β-lactamaseproducing strains of both gram-positive and gram-negative aerobes, facultative anaerobes, and obligate anaerobes. Many strains of the following organisms, including β-lactamase-producing strains, isolated from veterinary sources, were found to be susceptible to amoxicillin/ clavulanate in vitro but the clinical significance of this activity has not been demonstrated for some of these organisms in animals.

Aerobic bacteria, including Staphylococcus aureus^1 , β-lactamase producing Staphylococcus aureus^1 (penicillin resistant), Staphylococcus species^1 , Staphylococcus epidermidis, Staphylococcus intermedius, Streptococcus faecalis, Streptococcus species^1 , Corynebacterium pyogenes, Corynebacterium species, Erysipelothrix rhusiopathiae, Bordetella bronchiseptica, Escherichia coli^1 , Proteus mirabilis, Proteus species, Enterobacter species, Klebsiella pneumoniae, Salmonella dublin, Salmonella typhimurium, Pasteurella multocida, Pasteurella haemolytica, Pasteurella species^1

^1The susceptibility of these organisms has also been demonstrated in in vivo studies.

Studies have demonstrated that both aerobic and anaerobic flora are isolated from gingival cultures of dogs with clinical evidence of peridontal disease. Both gram-positive and gram-negative aerobic and anaerobic subgingival isolates indicate sensitivity to amoxicillin/ clavulanic acid during antimicrobial susceptibility testing.

SUSCEPTIBILITY TEST: The recommended quantitative disc susceptibility method (FEDERAL REGISTER 37:20527-29; Bauer AW, Kirby WMM, Sherris JC, et al: Antibiotic susceptibility testing by standardized single disc method. Am J Clin Path 45:493, 1966) utilized 30 mcg Augmentin® (AMC) discs for estimating the susceptibility of bacteria to amoxicillin and clavulanate potassium tablets.

INDICATIONS AND USAGE

INDICATIONS: Amoxicillin and Clavulanate Potassium Tablets are indicated in the treatment of:

Dogs: Skin and soft tissue infections such as wounds, abscesses, cellulitis, superficial/juvenile and deep pyoderma due to susceptible strains of the following organisms: β-lactamase-producing Staphylococcus aureus, non-β-lactamase-producing Staphylococcus aureus, Staphylococcus spp., Streptococcus spp., and E. coli.

Periodontal infections due to susceptible strains of both aerobic and anaerobic bacteria. Amoxicillin and clavulanate potassium tablets have been shown to be clinically effective for treating cases of canine periodontal disease.

Cats: Skin and soft tissue infections such as wounds, abscesses, and cellulitis/dermatitis due to susceptible strains of the following organisms: β-lactamase-producing Staphylococcus aureus, non- β-lactamase-producing Staphylococcus aureus, Staphylococcus spp., Streptococcus spp., E. coli, and Pasteurella spp. Urinary tract infections (cystitis) due to susceptible strains of E. coli.

Therapy may be initiated with Amoxicillin and Clavulanate Potassium Tablets prior to obtaining results from bacteriological and susceptibility studies. A culture should be obtained prior to treatment to determine susceptibility of the organisms to Amoxicillin and Clavulanate Potassium Tablets. Following determination of susceptibility results and clinical response to medication, therapy may be reevaluated.

CONTRAINDICATIONS

CONTRAINDICATIONS: The use of this drug is contraindicated in animals with a history of an allergic reaction to any of the penicillins or cephalosporins.

WARNINGS

WARNINGS: Safety of use in pregnant or breeding animals has not been determined. Store at controlled room temperature, 68-77°F (20-25°C).
Do not remove from foil strip until ready to use.

Keep Amoxicillin and Clavulanate Potassium Tablets in a secure location out of reach of dogs, cats, and other animals to prevent accidental ingestion or overdose.

ADVERSE REACTIONS

ADVERSE REACTIONS: Amoxicillin and Clavulanate Potassium Tablets contain a semisynthetic penicillin (amoxicillin) and has the potential for
producing allergic reactions. If an allergic reaction occurs, administer epinephrine and/or steroids.

Post-Approval Experience (July, 2017):
The following adverse events are based on the post-approval adverse drug experience reporting. Not all adverse events are reported to FDA/CVM. It is not always possible to reliably estimate the adverse event frequency or establish a casual relationship to product exposure using these data.
The following adverse events reported for dogs and cats are listed in decreasing order of reporting frequency for amoxicillin and clavulanate potassium tablets: Anorexia, lethargy, vomiting and diarrhea.
To report suspected adverse events, for technical assistance or to obtain a copy of the Safety Data Sheet, contact Cronus Pharma LLC at 1-844-227- 6687 (1-844-2-CRONUS). For additional information about adverse drug experience reporting for animal drugs, contact FDA at 1-888-FDA-VETS or http://www.fda.gov/reportanimalae.

DOSAGE AND ADMINISTRATION:

Dogs: The recommended dosage is 6.25 mg/lb of body weight twice a day.

Skin and soft tissue infections such as abscesses, cellulitis, wounds, superficial/juvenile pyoderma, and periodontal infections should be treated for 5-7 days or for 48 hours after all symptoms have subsided. If no response is seen after 5 days of treatment, therapy should be discontinued and the case reevaluated. Deep pyoderma may require treatment for 21 days; the maximum duration of treatment should not exceed 30 days.

Cats: The recommended dosage is 62.5 mg twice a day Skin and soft tissue infections such as abscesses and cellulitis/dermatitis should be treated for 5-7 days or for 48 hours after all symptoms have subsided, not to exceed 30 days. If no response is seen after 3 days of treatment, therapy should be discontinued and the case reevaluated.

Urinary tract infections may require treatment for 10-14 days or longer. The maximum duration of treatment should not exceed 30 days.

HOW SUPPLIED

HOW SUPPLIED: Amoxicillin and Clavulanate Potassium Tablets in the following strengths are supplied in strip packs. Each strip contains 14 tablets. Cartons with 5 strips (70 tablets per carton) and 15 strips (210 tablets per carton) are available.

Each 62.5-mg tablet contains amoxicillin trihydrate equivalent to 50 mg of amoxicillin activity and 12.5 mg of clavulanic acid as the potassium salt.
For use in dogs and cats.

Each 125-mg tablet contains amoxicillin trihydrate equivalent to 100 mg of amoxicillin activity and 25 mg of clavulanic acid as the potassium salt.
For use in dogs only.

Each 250-mg tablet contains amoxicillin trihydrate equivalent to 200 mg of amoxicillin activity and 50 mg of clavulanic acid as the potassium salt.
For use in dogs only.

Each 375-mg tablet contains amoxicillin trihydrate equivalent to 300 mg of amoxicillin activity and 75 mg of clavulanic acid as the potassium salt.
For use in dogs only.

Dispense according to recommendations outlined in Dosage and Administration section.

Augmentin is a trademark owned by GlaxoSmithKline.

Approved by FDA under ANADA # 200-702

Manufactured for:
Cronus Pharma LLC,
East Brunswick, NJ 08816.
Contact No: 1-844-227-6687
(1-844-2-CRONUS)
P1537018
Made in India
Revised: May 2024

PACKAGE LABEL.PRINCIPAL DISPLAY PANEL

NDC 69043-020-21

Amoxicillin and Clavulanate Potassium Tablets

62.5 mg

Veterinary Tablets

For use in dogs and cats

Caution: Federal law restricts this drug to use by or on the order of a licensed veterinarian.

Each film-coated tablet contains amoxicillin trihydrate equivalent to 50 mg of amoxicillin USP activity and 12.5 mg of clavulanic acid USP as the potassium salt

Approved by FDA under ANADA # 200-702

15 strips 14 tablets each

210 tablets

PACKAGE LABEL.PRINCIPAL DISPLAY PANEL

NDC 69043-021-21

Amoxicillin and Clavulanate Potassium Tablets

125 mg

Veterinary Tablets

For use in dogs

Caution: Federal law restricts this drug to use by or on the order of a licensed veterinarian.

Each film-coated tablet contains amoxicillin trihydrate equivalent to 100 mg of amoxicillin USP activity and 25 mg of clavulanic acid USP as the potassium salt

Approved by FDA under ANADA # 200-702

15 strips 14 tablets each

210 tablets

PACKAGE LABEL.PRINCIPAL DISPLAY PANEL

NDC 69043-022-21

Amoxicillin and Clavulanate Potassium Tablets

250 mg

Veterinary Tablets

For use in dogs

Caution: Federal law restricts this drug to use by or on the order of a licensed veterinarian.

Each film-coated tablet contains amoxicillin trihydrate equivalent to 200 mg of amoxicillin USP activity and 50 mg of clavulanic acid USP as the potassium salt

Approved by FDA under ANADA # 200-702

15 strips 14 tablets each

210 tablets

PACKAGE LABEL.PRINCIPAL DISPLAY PANEL

NDC 69043-023-21

Amoxicillin and Clavulanate Potassium Tablets

375 mg

Veterinary Tablets

For use in dogs

Caution: Federal law restricts this drug to use by or on the order of a licensed veterinarian.

Each film-coated tablet contains amoxicillin trihydrate equivalent to 300 mg of amoxicillin USP activity and 75 mg of clavulanic acid USP as the potassium salt

Approved by FDA under ANADA # 200-702

15 strips 14 tablets each

210 tablets